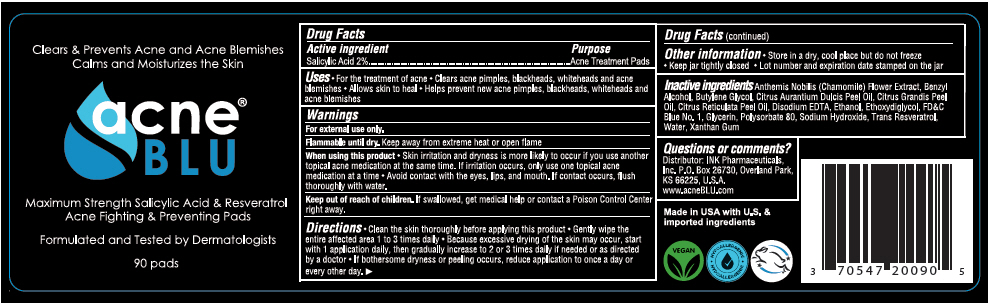 DRUG LABEL: Acne Blu Salicylic Acid Pads
NDC: 70547-200 | Form: DISC
Manufacturer: INK Pharmaceuticals, Inc.
Category: otc | Type: HUMAN OTC DRUG LABEL
Date: 20221227

ACTIVE INGREDIENTS: SALICYLIC ACID 20 g/1000 g
INACTIVE INGREDIENTS: WATER; SODIUM HYDROXIDE; EDETATE DISODIUM; GLYCERIN; XANTHAN GUM; DIETHYLENE GLYCOL MONOETHYL ETHER; ALCOHOL; FD&C BLUE NO. 1; BENZYL ALCOHOL; POLYSORBATE 80; RESVERATROL; CHAMAEMELUM NOBILE FLOWER; MEDIUM-CHAIN TRIGLYCERIDES; ORANGE PEEL; CITRUS MAXIMA FRUIT RIND OIL; MANDARIN OIL

INK Pharmaceuticals Acne Blu Salicylic Acid Pads 90 pads

Warnings

For external use only

Flammable until dry, keep away from extreme heat or open flame

When using this product skin irritation and dryness is more likely to occur if you use another topical acne medication at the same time. If irritation occurs, only use one topical acne medication at a time. Avoid contact with the eyes, lips and mouth. If contact occurs flush throughly with water.

If swallowed, get medical help or contact a Poison Control Center right away.

Keep out of reach of children

Active Ingredients

Salicylic Acid 2% Acne Treatment Pads

Uses

PURPOSE

For the treatment of acne. Clears acne pimples, blackheads, whiteheads and acne blemishes. Allows skin to heal. Helps prevent new acne pimples, blackheads, whiteheads and acne blemishes.

Directions

Clean the skin thoroughly before applying this product. Gently wipe the entire affected area 1 to 3 times daily. Because excessive drying of the skin may occur, start with 1 application daily, then gradually increase to 2 or 3 times daily if needed or as directed by a doctor. If bothersome dryness or peeling occurs, reduce application to once a day or every other day.

Other Information

Store in a dry, cool place but do not freeze. Keep jar tightly closed

Inactive Ingredients

Anthemis Nobilis (Chamomile) Flower Extract, Benzyl Alcohol, Butylene Glycol, Caprylic/Capric Triglycerides, Citrus Aurantium Dulcis Peel Oil, Citrus Grandis Peel Oil, Citrus Reticulata Peel Oil, Disodium EDTA, Ethanol, Ethoxydiglycol, FD&C Blue #1, Glycerin, Polysorbate 80, Sodium Hydroxide, Trans Resveratrol, Water, Xanthan Gum

Questions or comments?

INK Pharmaceuticals, Inc. PO Box 26730, Overland Park, KS 66225, USA

www.acneBLU.com

PRINCIPAL DISPLAY PANEL - 90 Pad Jar Label

Clears & Prevents Acne and Acne Blemishes
Calms and Moisturizes the Skin

acne®
BLU

Maximum Strength Salicylic Acid & Resveratrol
Acne Fighting & Preventing Pads

Formulated and Tested by Dermatologists

90 pads